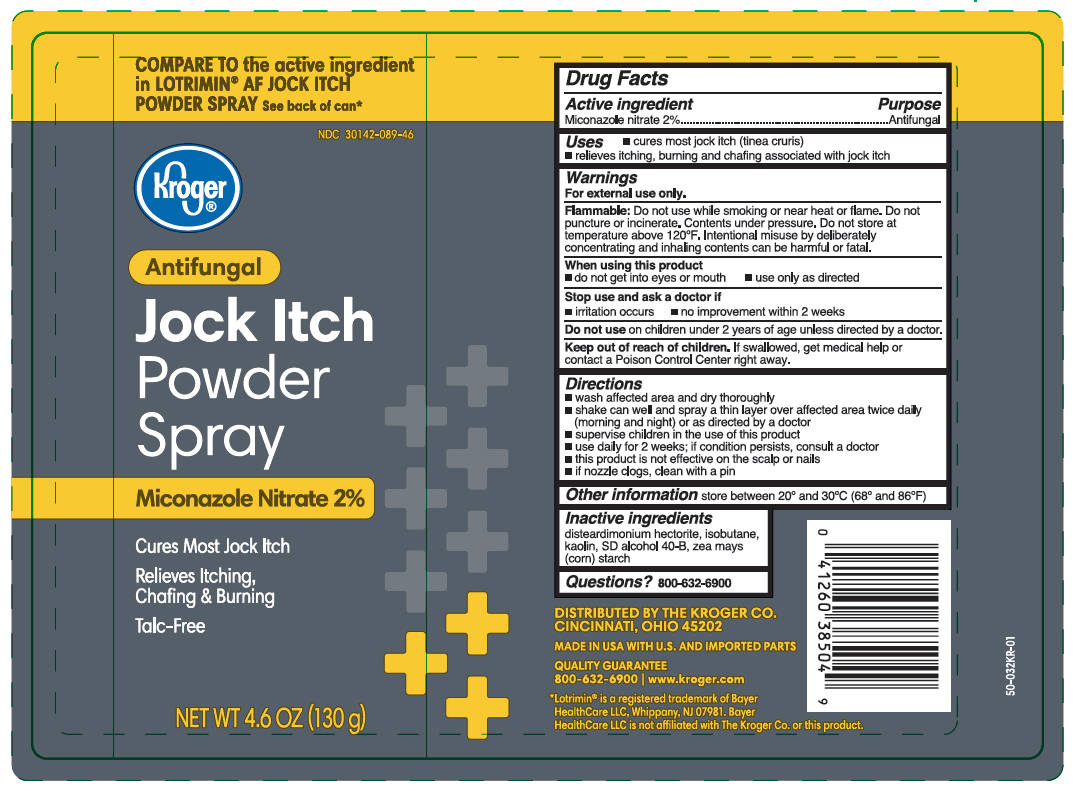 DRUG LABEL: Miconazole Nitrate
NDC: 30142-089 | Form: AEROSOL, SPRAY
Manufacturer: Kroger Co.
Category: otc | Type: HUMAN OTC DRUG LABEL
Date: 20251030

ACTIVE INGREDIENTS: MICONAZOLE NITRATE 1.3 g/130 g
INACTIVE INGREDIENTS: KAOLIN; DISTEARDIMONIUM HECTORITE; ISOBUTANE; ALCOHOL; STARCH, CORN

Kroger Antifungal Jock Itch Powder Spray

Active ingredient

Miconazole nitrate 2%

Purpose

Antifungal

Uses

- cures most jock itch (tinea cruris)
- relieves itching, burning and chafing associated with jock itch

Warnings

For external use only.

Flammable:

Do not use while smoking or near heat or flame. Do not puncture or incinerate. Contents under pressure. Do not store at temperature above 120°F. Intentional misuse by deliberately concentrating and inhaling contents can be harmful or fatal.

When using this product

- do not get into eyes or mouth
- use only as directed

Stop use and ask a doctor if

- irritiation occurs
- no improvement within 2 weeks

Do not use

on children under 2 years of age unless directed by a doctor.

Keep out of reach of children.

If swallowed, get medical help or contact a Poison Control Center right away.

Directions

- wash affected area and dry thoroughly
- shake can well and spray a thin layer over affected area twice daily

(morning and night) or as directed by a doctor

- supervise children in the use of this product
- use daily for two weeks; if condition persists, consult a doctor
- this product is not effective on the scalp or nails
- if nozzle clogs, clean with a pin

Other information

store between 20° and 30°C (68° and 86°F)

Inactive ingredients

disteardimonium hectorite, isobutane, kaolin, SD alcohol 40-B, zea mays (corn) starch

Questions?

800-632-6900

Principal Display Panel

Kroger

Antifungal

Jock Itch

Powder

Spray

Miconazole Nitrate 2%

Cures Most Jock Itch

Relieves Itching,

Chafing & Burning

Talc-Free

NET WT 4.6 OZ(130g)